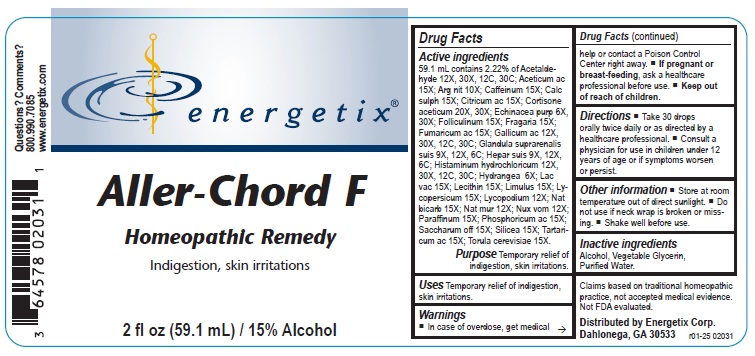 DRUG LABEL: Aller-Chord F
NDC: 64578-0148 | Form: LIQUID
Manufacturer: Energetix Corporation
Category: homeopathic | Type: HUMAN OTC DRUG LABEL
Date: 20250715

ACTIVE INGREDIENTS: ACETALDEHYDE 12 [hp_X]/59.1 mL; SUS SCROFA ADRENAL GLAND 9 [hp_X]/59.1 mL; SILVER NITRATE 10 [hp_X]/59.1 mL; CORTISONE ACETATE 20 [hp_X]/59.1 mL; GALLIC ACID MONOHYDRATE 12 [hp_X]/59.1 mL; HISTAMINE DIHYDROCHLORIDE 12 [hp_X]/59.1 mL; ECHINACEA PURPUREA 6 [hp_X]/59.1 mL; HYDRANGEA ARBORESCENS ROOT 6 [hp_X]/59.1 mL; PORK LIVER 9 [hp_X]/59.1 mL; LYCOPODIUM CLAVATUM SPORE 12 [hp_X]/59.1 mL; STRYCHNOS NUX-VOMICA SEED 12 [hp_X]/59.1 mL; ACETIC ACID 15 [hp_X]/59.1 mL; CAFFEINE 15 [hp_X]/59.1 mL; CALCIUM SULFATE ANHYDROUS 15 [hp_X]/59.1 mL; ANHYDROUS CITRIC ACID 15 [hp_X]/59.1 mL; FUMARIC ACID 15 [hp_X]/59.1 mL; COW MILK 15 [hp_X]/59.1 mL; EGG PHOSPHOLIPIDS 15 [hp_X]/59.1 mL; SODIUM BICARBONATE 15 [hp_X]/59.1 mL; SUCROSE 15 [hp_X]/59.1 mL; TARTARIC ACID 15 [hp_X]/59.1 mL; SACCHAROMYCES CEREVISIAE 15 [hp_X]/59.1 mL; SODIUM CHLORIDE 12 [hp_X]/59.1 mL; PARAFFIN 15 [hp_X]/59.1 mL; ESTRONE 15 [hp_X]/59.1 mL; PHOSPHORIC ACID 15 [hp_X]/59.1 mL; ALPINE STRAWBERRY 15 [hp_X]/59.1 mL; LIMULUS POLYPHEMUS 15 [hp_X]/59.1 mL; SOLANUM LYCOPERSICUM 15 [hp_X]/59.1 mL; SILICON DIOXIDE 15 [hp_X]/59.1 mL
INACTIVE INGREDIENTS: ALCOHOL; GLYCERIN; WATER

Aller-Chord F

ACTIVE INGREDIENT

Active ingredients59.1 mL contains 2.22% of Acetaldehyde 12X, 30X, 12C, 30C; Aceticum ac 15X; Arg nit 10X; Caffeinum 15X; Calc sulph 15X; Citricum ac 15X; Cortisone aceticum 20X, 30X; Echinacea purp 6X, 30X; Folliculinum 15X; Fragaria 15X; Fumaricum ac 15X; Gallicum ac 12X, 30X, 12C, 30C; Glandula suprarenalis suis 9X, 12X, 6C; Hepar suis 9X, 12X, 6C; Histaminum hydrochloricum 12X, 30X, 12C, 30C; Hydrangea 6X; Lac vac 15X; Lecithin 15X; Limulus 15X; Lycopersicum 15X; Lycopodium 12X; Natrum bicarb 15X; Nat mur 12X; Nux vom 12X; Paraffinum 15X; Phosphoricum ac 15X; Saccharum off 15X; Silicea 15X; Tartaricum ac 15X; Torula cerevisiae 15X.

Claims based on traditional homeopathic practice, not accepted medical evidence. Not FDA evaluated.

Uses

Temporary relief of indigestion, skin irritations.

Warnings

- In case of overdose, get medical help or contact a Poison Control Center right away.
- If pregnant or breast feeding, ask a healthcare professional before use.

Keep out of reach of children.

Directions

- Take 30 drops orally twice daily or as directed by a healthcare professional.
- Consult a physician for use in children under 12 years or age or if symptoms worsen or persist.

Other information

- Store at room temperature out of direct sunlight.
- Do not use if neck wrap is broken or missing.
- Shake well before use.

Inactive ingredients

Alcohol, Vegetable Glycerin, Purified Water.

QUESTIONS

Distributed by Energetix Corp.

Dahlonega, GA 30533

Questions? 800.990.7085

www.energetix.com

PACKAGE LABEL

energetix

Aller-Chord F

Homeopathic Remedy

Ingestion, skin irritations

2 fl oz (59.1 mL) / 15% Alcohol

Purpose Temporary relief of indigestion, skin irritations.